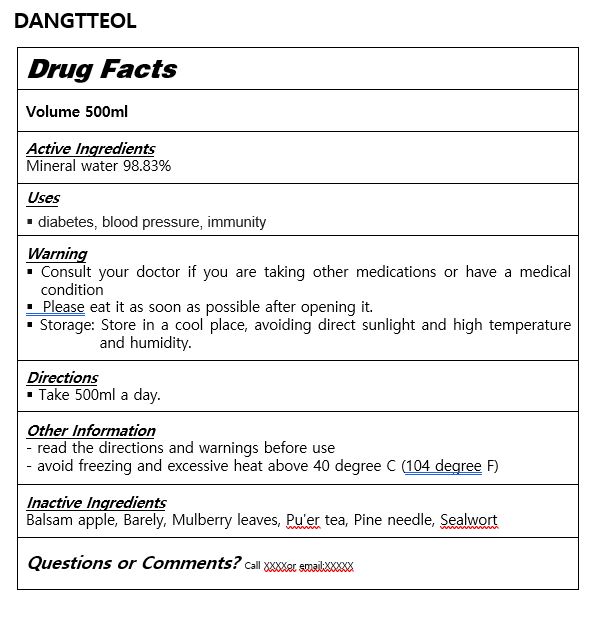 DRUG LABEL: DANGTTEOL
NDC: 84990-0001 | Form: LIQUID
Manufacturer: AQBC CO., LTD
Category: otc | Type: HUMAN OTC DRUG LABEL
Date: 20241126

ACTIVE INGREDIENTS: WATER 98.832 g/100 mL
INACTIVE INGREDIENTS: PINE NEEDLE OIL (PINUS MUGO)

ACTIVE INGREDIENT

mineral water

INACTIVE INGREDIENT

Balsam apple, Barely, Mulberry leaves, Pu'er tea, Pine needle, Sealwort

PURPOSE

diabetes, blood pressure, immunity

keep out of reach of the children

INDICATIONS AND USAGE

Take 500ml a day

WARNINGS

￭ Consult your doctor if you are taking other medications or have a medical condition

￭ Please eat it as soon as possible after opening it.

￭ Storage: Store in a cool place, avoiding direct sunlight and high temperature and humidity.

DOSAGE AND ADMINISTRATION

for oral use